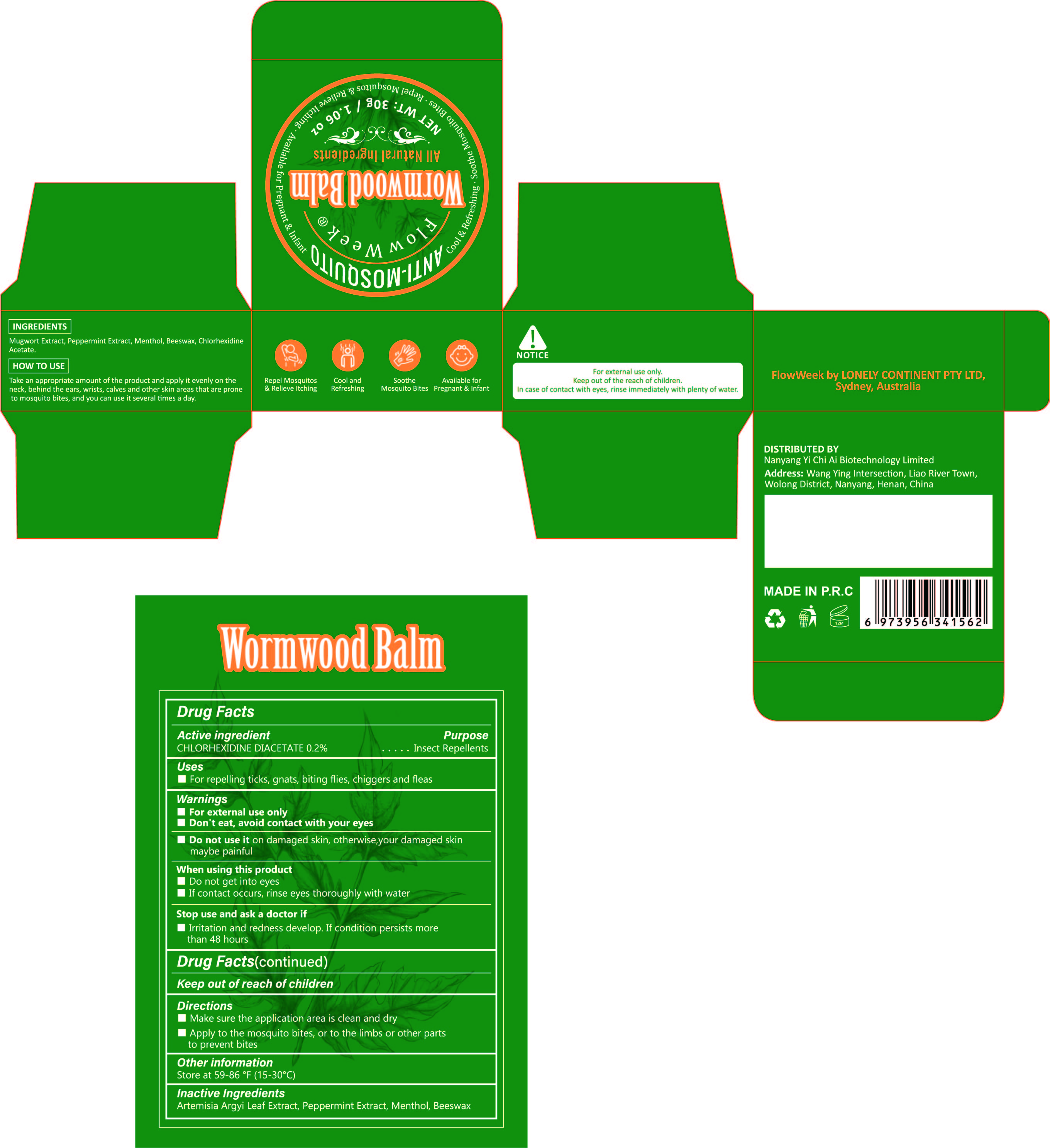 DRUG LABEL: WORMWOOD BALM
NDC: 84445-004 | Form: CREAM
Manufacturer: Shenzhen Furuizhilian keji Co., Ltd.
Category: otc | Type: HUMAN OTC DRUG LABEL
Date: 20240715

ACTIVE INGREDIENTS: MENTHOL 0.15 g/30 g
INACTIVE INGREDIENTS: CHLORHEXIDINE ACETATE; ARTEMISIA ARGYI LEAF; YELLOW WAX; PEPPERMINT

WORMWOOD BALM

ACTIVE INGREDIENT

MENTHOL 0.5%

PURPOSE

Insect Repellents

INDICATIONS AND USAGE

Make sure the application area is clean and dry.
Apply to the mosquito bites, or to the limbs or other parts to prevent bites.

WARNINGS

For external use only
Don't eat, avoid contact with your eyes.

STOP USE

irritation and redness develop. If condition persists more than 48 hours.

WHEN USING

Do not get into eyes.
If contact occurs, rinse eyes thoroughly with water.

KEEP OUT OF REACH OF CHILDREN

If swallowed, get medical help or contact a Poison Control Center right away.

INACTIVE INGREDIENT

Artemisia Argyi Leaf Extract, Peppermint Extract, Menthol, Beeswax